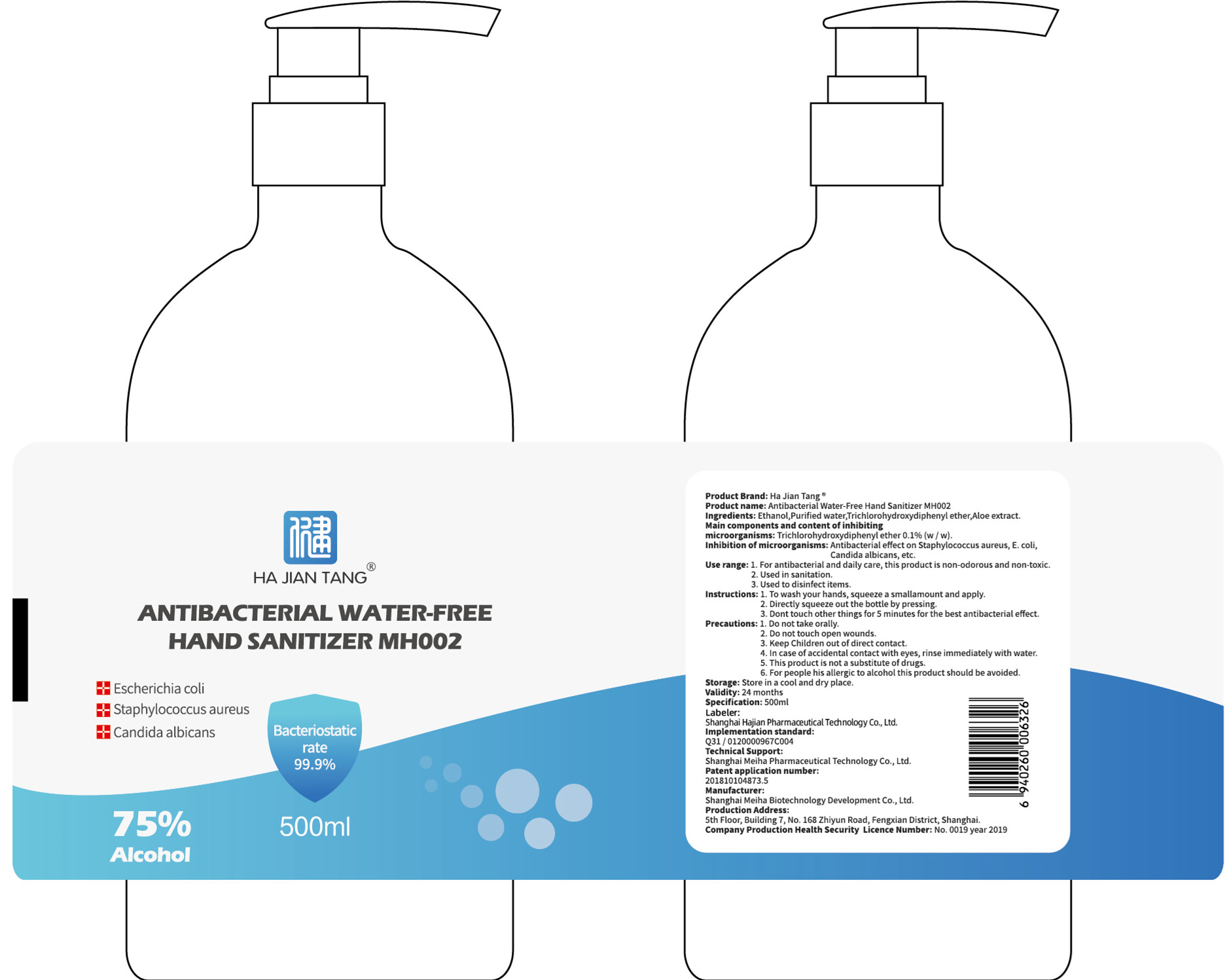 DRUG LABEL: HA JIAN TANG ANTIBACTERIAL WATER-FREE HAND SANITIZER
NDC: 55428-001 | Form: LIQUID
Manufacturer: Shanghai Hajian Pharmaceutical Technology Co., Ltd.
Category: otc | Type: HUMAN OTC DRUG LABEL
Date: 20200513

ACTIVE INGREDIENTS: ALCOHOL 375 mL/500 mL
INACTIVE INGREDIENTS: WATER; ALOE

DOSAGE AND ADMINISTRATION

Store in a cool and dry place.

INACTIVE INGREDIENT

Puifiled water

aloe extract

INDICATIONS AND USAGE

1. To wash your hands, squeeze a smallamount and apply.
2. Directly squeeze out the bottle by pressing.
3. Dont touch other things for 5 minutes for the best antibacterial effect.

ACTIVE INGREDIENT

Alcohol

keep out of reach of children

PURPOSE

Disinfection
Sterilization
No Rinseing

WARNINGS

1. Do not take orally.
2. Do not touch open wounds.
3. Keep Children out of direct contact.
4. In case of accidental contact with eyes, rinse immediately with water.
5. This product is not a substitute of drugs.
6. For people his allergic to alcohol this product should be avoided.